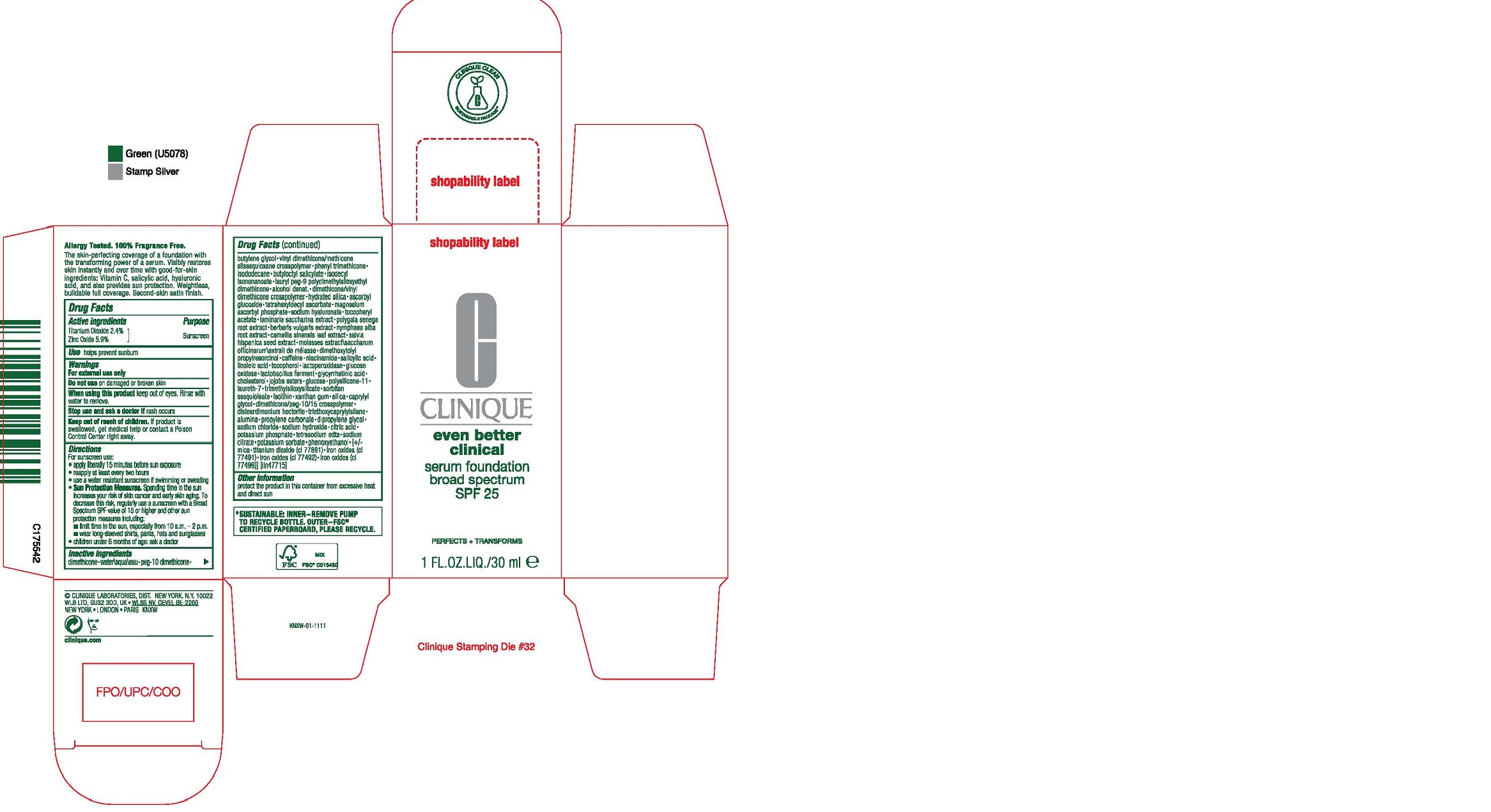 DRUG LABEL: CLINIQUE EVEN BETTER CLINICAL SERUM FOUNDATION BROAD SPECTRUM SPF 25
NDC: 49527-080 | Form: LIQUID
Manufacturer: CLINIQUE LABORATORIES LLC
Category: otc | Type: HUMAN OTC DRUG LABEL
Date: 20231019

ACTIVE INGREDIENTS: TITANIUM DIOXIDE 24 mg/1 mL; ZINC OXIDE 59 mg/1 mL
INACTIVE INGREDIENTS: NYMPHAEA ALBA ROOT; GREEN TEA LEAF; CHIA SEED; MOLASSES; DIMETHOXYTOLYL PROPYLRESORCINOL; CAFFEINE; NIACINAMIDE; SALICYLIC ACID; LINOLEIC ACID; TOCOPHEROL; MYELOPEROXIDASE; GLUCOSE OXIDASE; LIMOSILACTOBACILLUS REUTERI; ENOXOLONE; CHOLESTEROL; HYDROGENATED JOJOBA OIL, RANDOMIZED; ANHYDROUS DEXTROSE; DIMETHICONE/VINYL DIMETHICONE CROSSPOLYMER (SOFT PARTICLE); LAURETH-7; TRIMETHYLSILOXYSILICATE (M/Q 0.6-0.8); SORBITAN SESQUIOLEATE; EGG PHOSPHOLIPIDS; XANTHAN GUM; SILICON DIOXIDE; CAPRYLYL GLYCOL; DIMETHICONE PEG-15 ACETATE; DISTEARDIMONIUM HECTORITE; TRIETHOXYCAPRYLYLSILANE; ALUMINUM OXIDE; PROPYLENE CARBONATE; DIPROPYLENE GLYCOL; SODIUM CHLORIDE; SODIUM HYDROXIDE; CITRIC ACID MONOHYDRATE; POTASSIUM PHOSPHATE, UNSPECIFIED FORM; EDETATE SODIUM; SODIUM CITRATE, UNSPECIFIED FORM; POTASSIUM SORBATE; PHENOXYETHANOL; MICA; FERRIC OXIDE RED; WATER; DIMETHICONE; DIMETHICONE PEG-10 PHOSPHATE; BUTYLENE GLYCOL; VINYL DIMETHICONE/METHICONE SILSESQUIOXANE CROSSPOLYMER; PHENYL TRIMETHICONE; ISODODECANE; BUTYLOCTYL SALICYLATE; ISODECYL ISONONANOATE; LAURYL PEG-9 POLYDIMETHYLSILOXYETHYL DIMETHICONE; ALCOHOL; DIMETHICONE/VINYL DIMETHICONE CROSSPOLYMER (HARD PARTICLE); HYDRATED SILICA; ASCORBYL GLUCOSIDE; TETRAHEXYLDECYL ASCORBATE; MAGNESIUM ASCORBYL PHOSPHATE; HYALURONATE SODIUM; .ALPHA.-TOCOPHEROL ACETATE; SACCHARINA LATISSIMA; POLYGALA SENEGA ROOT; BERBERIS VULGARIS ROOT BARK

CLINIQUE EVEN BETTER CLINICAL SERUM FOUNDATION BROAD SPECTRUM SPF 25

Drug Facts

Active ingredients

Titanium Dioxide 2.4%

Zinc Oxide 5.9%

Purpose

Sunscreen

Use

helps prevent sunburn

Warnings

For external use only

Do not use on damaged or broken skin

When using this product keep out of eyes. Rinse with water to remove.

Stop use and ask a doctor if rash occurs

Keep out of reach of children. If product is swallowed, get medical help or contact a Poison Control Center right away.

Directions

For sunscreen use:

- apply liberally 15 minutes before sun exposure
- reapply at least every two hours
- use a water resistant sunscreen if swimming or sweating
- Sun Protection Measures. Spending time in the sun increases your risk of skin cancer and early skin aging. To decrease this risk, regularly use a sunscreen with a Broad Spectrum SPF value of 15 or higher and other sun protection measures including:
  - limit time in the sun, especially from 10 a.m. – 2 p.m.
  - wear long-sleeved shirts, pants, hats and sunglasses
- children under 6 months of age: ask a doctor

Inactive ingredients

dimethicone•water\aqua\eau•peg-10 dimethicone•butylene glycol•vinyl dimethicone/methicone silsesquioxane crosspolymer•phenyl trimethicone• isododecane•butyloctyl salicylate•isodecyl isononanoate•lauryl peg-9 polydimethylsiloxyethyl dimethicone•alcohol denat.•dimethicone/vinyl dimethicone crosspolymer•hydrated silica•ascorbyl glucoside•tetrahexyldecyl ascorbate•magnesium ascorbyl phosphate•sodium hyaluronate•tocopheryl acetate•laminaria saccharina extract•polygala senega root extract•berberis vulgaris extract•nymphaea alba root extract•camellia sinensis leaf extract•salvia hispanica seed extract•molasses extract\saccharum officinarum\extrait de mélasse•dimethoxytolyl propylresorcinol•caffeine•niacinamide•salicylic acid• linoleic acid•tocopherol•lactoperoxidase•glucose oxidase•lactobacillus ferment•glycyrrhetinic acid• cholesterol•jojoba esters•glucose•polysilicone-11• laureth-7•trimethylsiloxysilicate•sorbitan sesquioleate•lecithin•xanthan gum•silica•caprylyl glycol•dimethicone/peg-10/15 crosspolymer• disteardimonium hectorite•triethoxycaprylylsilane• alumina•propylene carbonate•dipropylene glycol• sodium chloride•sodium hydroxide•citric acid• potassium phosphate•tetrasodium edta•sodium citrate•potassium sorbate•phenoxyethanol•[+/-mica•titanium dioxide (ci 77891)•iron oxides (ci 77491)•iron oxides (ci 77492)•iron oxides (ci 77499)] [iln47715]

Other information

protect the product in this container from excessive heat and direct sun

PRINCIPAL DISPLAY PANEL - 30 ml Bottle Carton

CLINIQUE

even better
clinical

serum foundation
broad spectrum
SPF 25

PERFECTS + TRANSFORMS

1 FL.OZ.LIQ./30 ml ℮